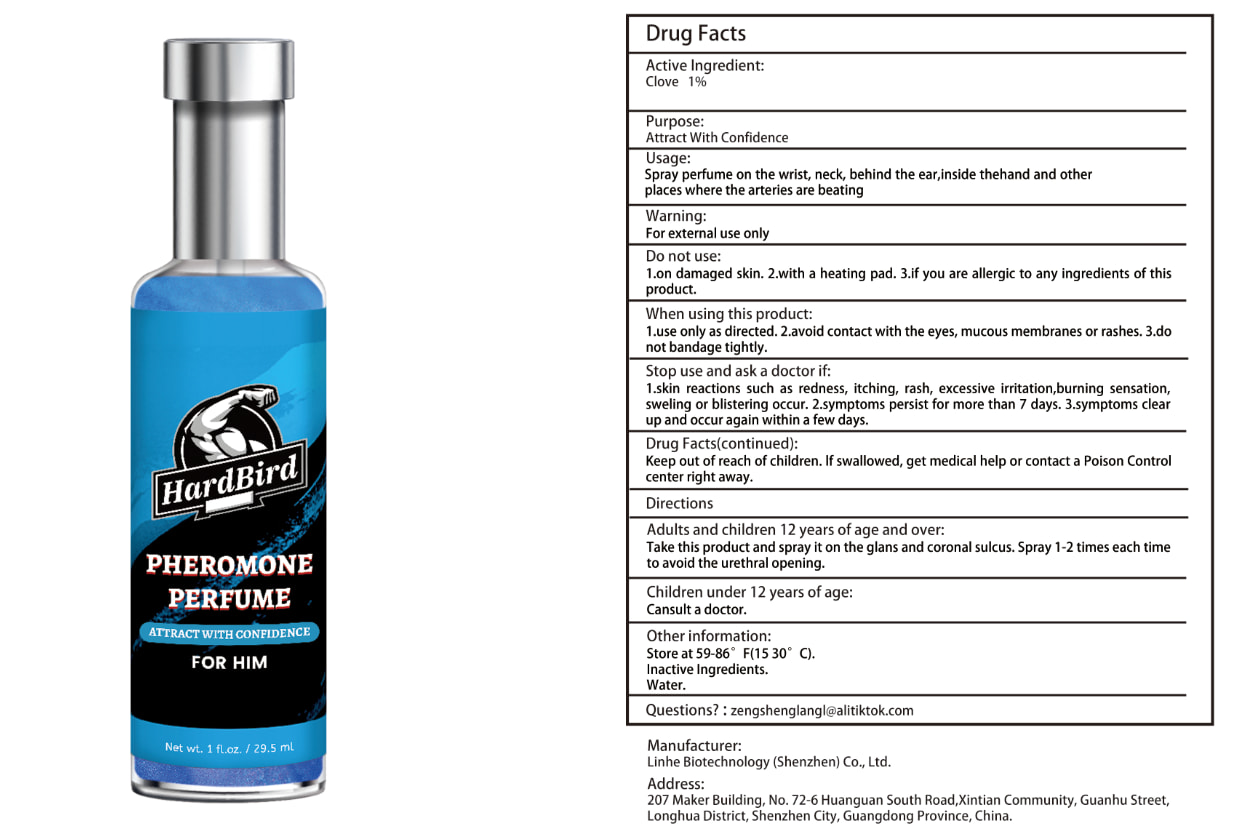 DRUG LABEL: Pheromone Perfume For Him
NDC: 84575-007 | Form: LIQUID
Manufacturer: Linhe Biotechnology (Shenzhen) Co., Ltd
Category: otc | Type: HUMAN OTC DRUG LABEL
Date: 20240820

ACTIVE INGREDIENTS: CLOVE 1 g/12 mL
INACTIVE INGREDIENTS: WATER

Pheromone Perfume For Him

ACTIVE INGREDIENT

Clove 1%

PURPOSE

Attract With Confidence

INDICATIONS AND USAGE

Spray perfume on the wrist, neck, behind the ear,inside thehand and other places where the arteries are beating

WARNINGS

For external use only.
Patients with renal failure and those with low heart rates should not use this product. This product is notintended to diagnose,treat, cure or prevent any disease.

DOSAGE AND ADMINISTRATION

Take this product and spray it on the glans and coronal sulcus. Spray 1-2 times each time to avoid the urethral opening.

INACTIVE INGREDIENT

WATER

STORAGE AND HANDLING

Store in a cool and dark place away from light

Keep out of reach of children,in case of overdose, get medical help or contact a PoisonControl Center right away.